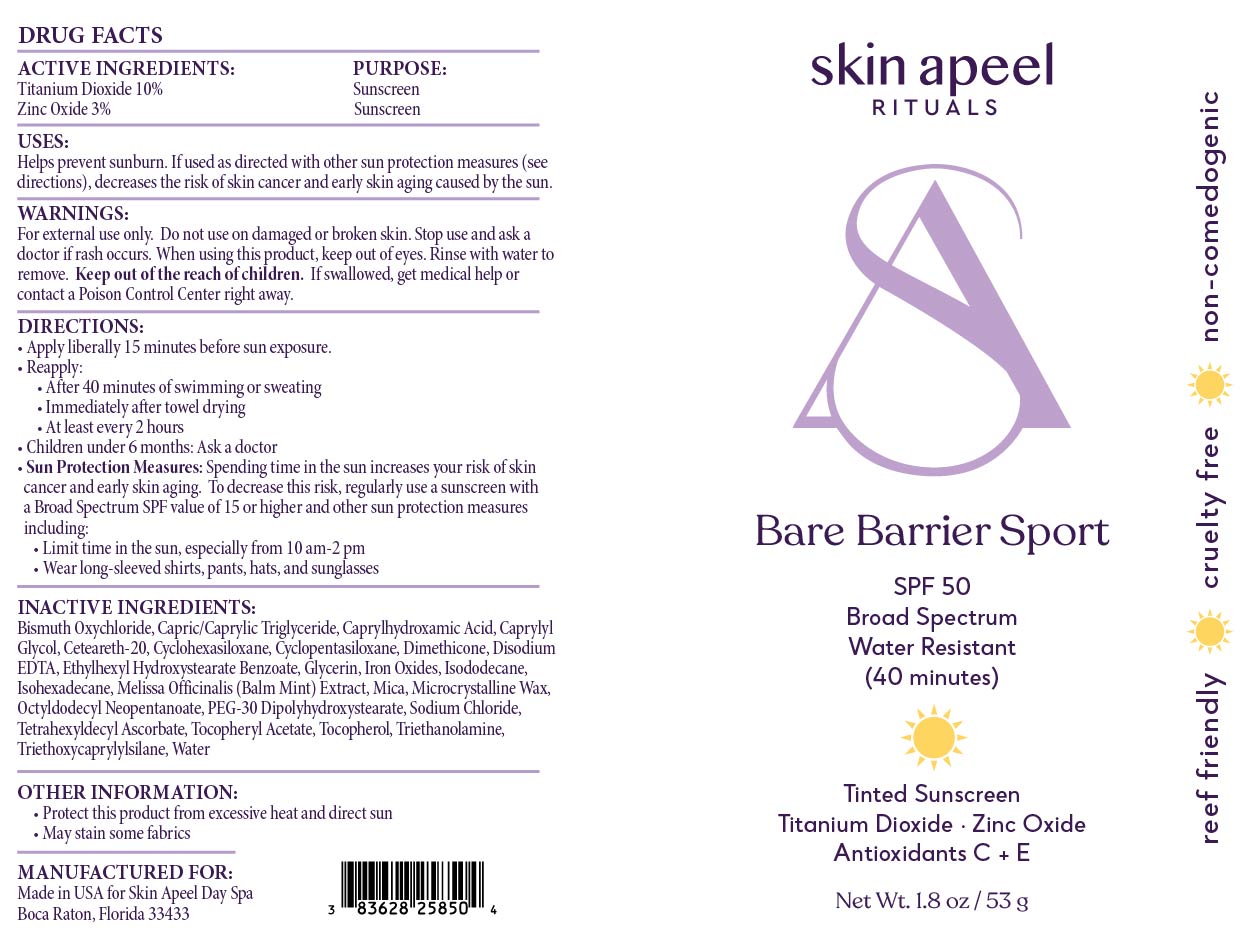 DRUG LABEL: Bare Barrier Sport
NDC: 83628-258 | Form: CREAM
Manufacturer: Skin Apeel, Inc.
Category: otc | Type: HUMAN OTC DRUG LABEL
Date: 20251208

ACTIVE INGREDIENTS: ZINC OXIDE 30 mg/1 g; TITANIUM DIOXIDE 100 mg/1 g
INACTIVE INGREDIENTS: CI 77499; MELISSA OFFICINALIS LEAF; CETEARETH-20; OCTYLDODECYL NEOPENTANOATE; CI 77492; SODIUM CHLORIDE; TRIETHOXYCAPRYLYLSILANE; GLYCERIN; ISODODECANE; TOCOPHEROL; WATER; CAPRYLHYDROXAMIC ACID; ETHYLHEXYL HYDROXYSTEARATE BENZOATE; CAPRYLIC/CAPRIC TRIGLYCERIDE; CI 77491; BISMUTH OXYCHLORIDE; CYCLOHEXASILOXANE; CYCLOPENTASILOXANE; DIMETHICONE; TRIETHANOLAMINE; PEG-30 DIPOLYHYDROXYSTEARATE; ALPHA-TOCOPHEROL ACETATE; CAPRYLYL GLYCOL; EDETATE DISODIUM ANHYDROUS; ISOHEXADECANE; MICA; MICROCRYSTALLINE WAX; TETRAHEXYLDECYL ASCORBATE

Active Ingredients:

Titanium Dioxide 10%

Zinc Oxide 3%

Purpose:

Sunscreen

Uses:

Helps Prevent Sunburn. If used as directed with other sun protection measures (see “Directions”), decreases the risk of skin cancer and early skin aging caused by the sun.

Warnings:

For external use only. Do not use on broken or damaged skin. Stop use and ask a doctor if rash occurs. When using this product, keep out of eyes. Rinse with water to remove. Keep out of reach of children. If swallowed, get medical help or contact a poison control center right away.

Warnings:

Keep out of reach of children

Directions:

Apply liberally 15 minutes before sun exposure. Use a water-resistant product if swimming or sweating. Reapply at least every 2 hours. Children under 6 months: Ask a doctor. Sun Protection Measures: Spending time in the sun increases your risk of skin cancer and early skin aging. To decrease this risk, regularly use a sunscreen with a Broad-Spectrum SPF value of 15 or higher and other sun protection measures including: Limit time in the sun, especially from 10 a.m. - 2 p.m. Wear long-sleeved shirts, pants, hats and sunglasses.

Inactive Ingredients:

Bismuth Oxychloride, Capric/Caprylic Triglyceride, Caprylhydroxamic Acid, Caprylyl Glycol, Ceteareth-20, Cyclohexasiloxane, Cyclopentasiloxane, Dimethicone, Disodium EDTA, Ethylhexyl Hydroxystearate Benzoate, Glycerin, Iron Oxides, Isododecane, Isohexadecane, Melissa Officinalis (Balm Mint) Extract, Mica, Microcrystalline Wax, Octyldodecyl Neopentanoate, PEG-30 Dipolyhydroxystearate, Sodium Chloride, Tetrahexyldecyl Ascorbate, Tocopheryl Acetate, Tocopherol, Triethanolamine, Triethoxycaprylylsilane, Water

Other Information:

- Protect this product from excessive heat and direct sun
- May stain some fabrics